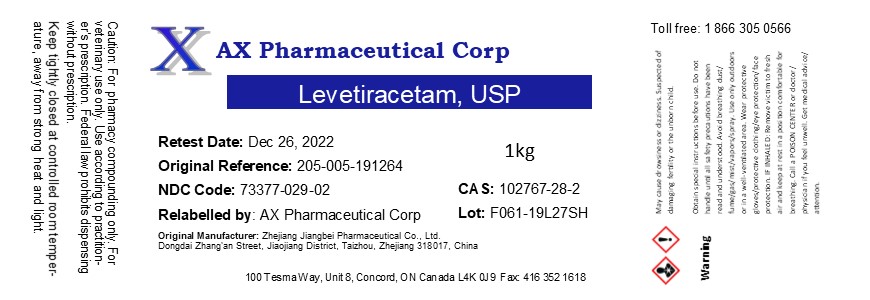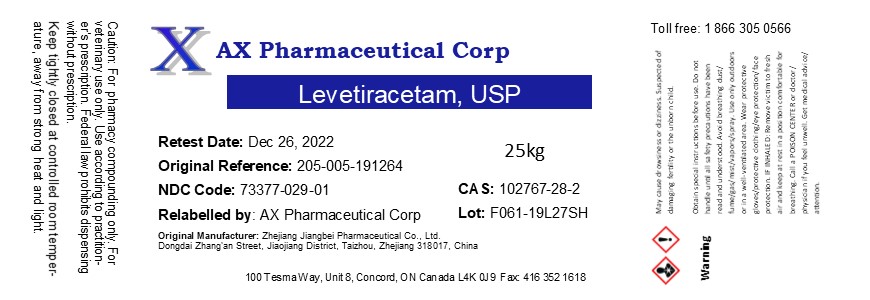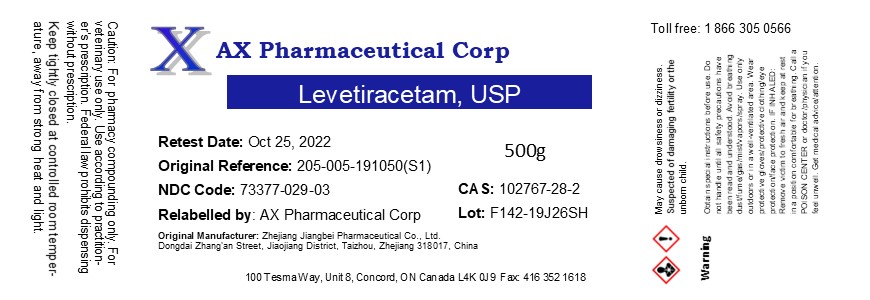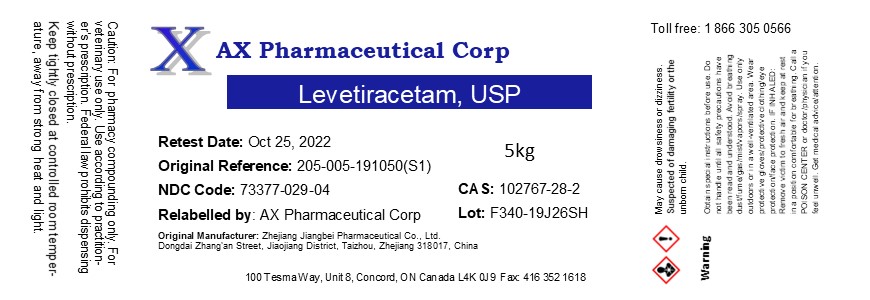 DRUG LABEL: Levetiracetam
NDC: 73377-029 | Form: POWDER
Manufacturer: AX Pharmaceutical Corp
Category: other | Type: BULK INGREDIENT
Date: 20200728

ACTIVE INGREDIENTS: LEVETIRACETAM 1 kg/1 kg

Levetiracetam